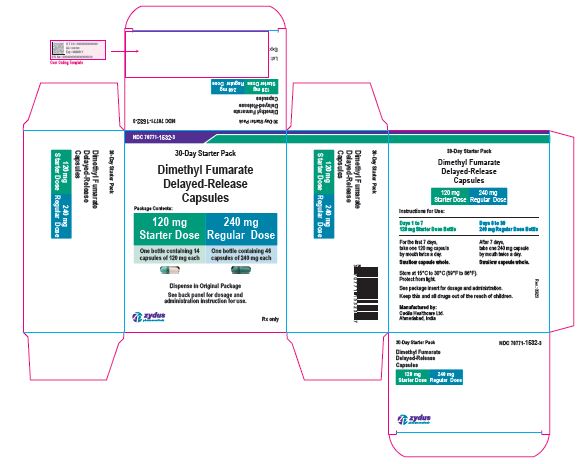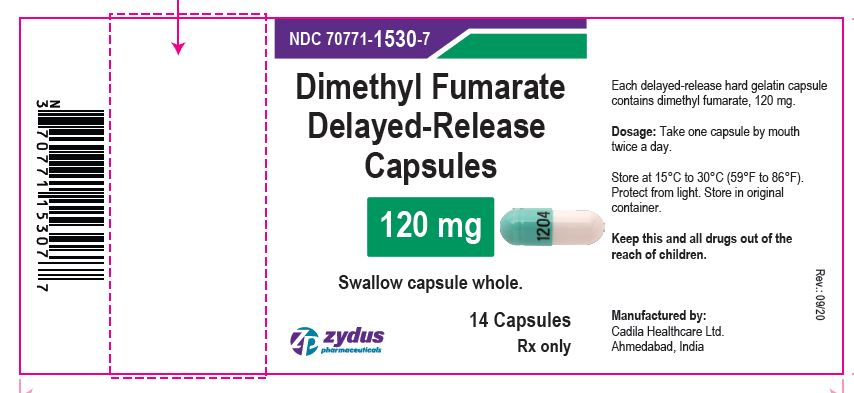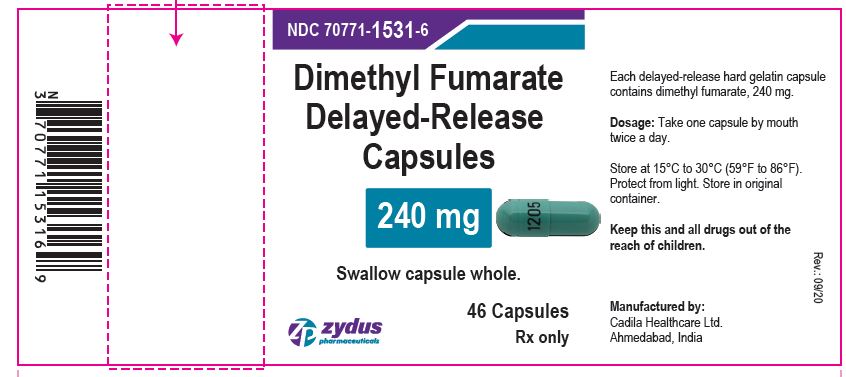 DRUG LABEL: dimethyl fumarate

NDC: 70771-1532 | Form: KIT | Route: ORAL
Manufacturer: Zydus Lifesciences Limited
Category: prescription | Type: HUMAN PRESCRIPTION DRUG LABEL
Date: 20250401

ACTIVE INGREDIENTS: DIMETHYL FUMARATE 120 mg/1 1; DIMETHYL FUMARATE 240 mg/1 1
INACTIVE INGREDIENTS: AMMONIA; CELLULOSE, MICROCRYSTALLINE; CROSCARMELLOSE SODIUM; D&C YELLOW NO. 10; FD&C BLUE NO. 1; FD&C RED NO. 40; FERRIC OXIDE RED; FERRIC OXIDE YELLOW; FERROSOFERRIC OXIDE; GELATIN; GLYCERYL MONO- AND DICAPRYLOCAPRATE; MAGNESIUM STEARATE; METHACRYLIC ACID - METHYL METHACRYLATE COPOLYMER (1:1); METHACRYLIC ACID AND ETHYL ACRYLATE COPOLYMER; POLYSORBATE 80; POTASSIUM HYDROXIDE; POVIDONE K30; PROPYLENE GLYCOL; SHELLAC; SILICON DIOXIDE; SODIUM LAURYL SULFATE; TALC; TITANIUM DIOXIDE; TRIETHYL CITRATE; AMMONIA; CELLULOSE, MICROCRYSTALLINE; CROSCARMELLOSE SODIUM; D&C YELLOW NO. 10; FD&C BLUE NO. 1; FD&C RED NO. 40; FERRIC OXIDE RED; FERRIC OXIDE YELLOW; FERROSOFERRIC OXIDE; GELATIN; GLYCERYL MONO- AND DICAPRYLOCAPRATE; MAGNESIUM STEARATE; METHACRYLIC ACID - METHYL METHACRYLATE COPOLYMER (1:1); METHACRYLIC ACID AND ETHYL ACRYLATE COPOLYMER; POLYSORBATE 80; POTASSIUM HYDROXIDE; POVIDONE K30; PROPYLENE GLYCOL; SHELLAC; SILICON DIOXIDE; SODIUM LAURYL SULFATE; TALC; TITANIUM DIOXIDE; TRIETHYL CITRATE

DIMETHYL FUMARATE DELAYED-RELEASE CAPSULES

PACKAGE LABEL.PRINCIPAL DISPLAY PANEL

NDC 70771-1532-3

30-Day Starter Pack Carton Label

Dimethyl Fumarate Delayed-release Capsules

120 mg Starter Dose: 14 Capsules

240 mg Regular Dose: 46 Capsules

Rx only

NDC 70771-1530-7

Dimethyl Fumarate Delayed-release Capsules, 120 mg

14 Capsules

Rx only

NDC 70771-1531-6

Dimethyl Fumarate Delayed-release Capsules, 240 mg

60 Capsules

Rx only